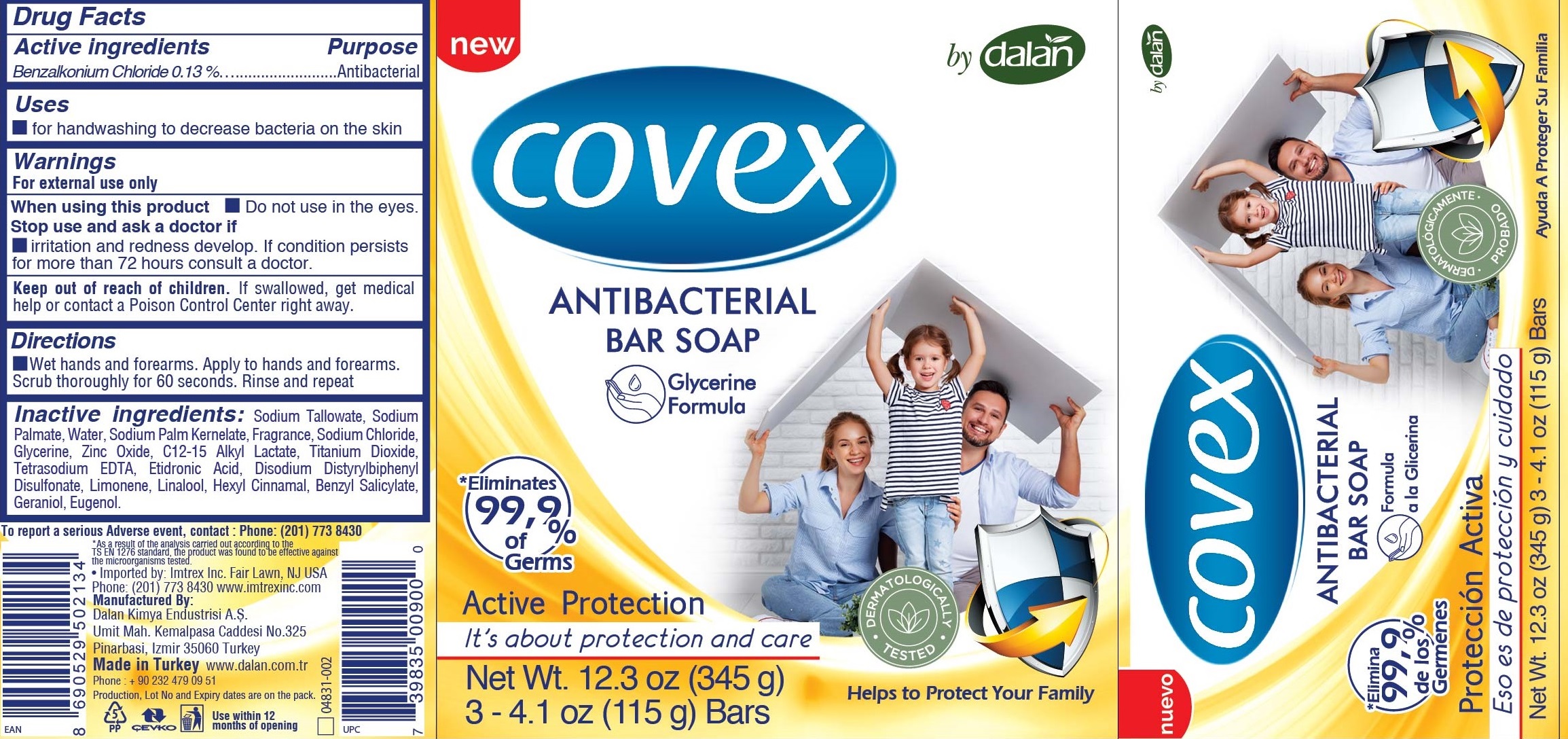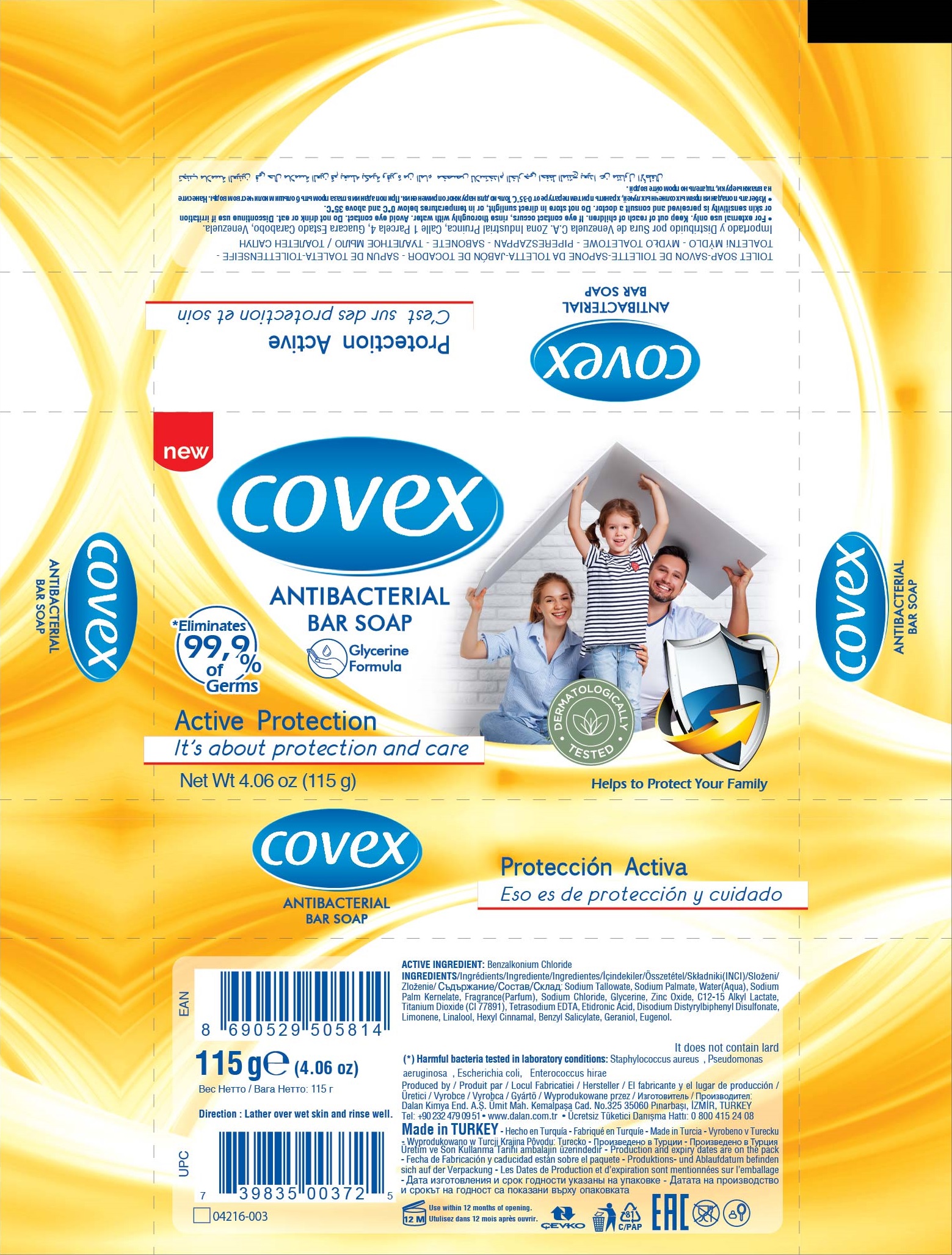 DRUG LABEL: Covex Antibacterial Bar Active Protection
NDC: 51209-017 | Form: SOAP
Manufacturer: DALAN KIMYA ENDUSTRI ANONIM SIRKETI
Category: otc | Type: HUMAN OTC DRUG LABEL
Date: 20210127

ACTIVE INGREDIENTS: BENZALKONIUM CHLORIDE 1.3 mg/1 g
INACTIVE INGREDIENTS: SODIUM TALLOWATE, BEEF; SODIUM PALMATE; WATER; SODIUM PALM KERNELATE; SODIUM CHLORIDE; GLYCERIN; C12-15 ALKYL LACTATE; TITANIUM DIOXIDE; EDETATE SODIUM; ETIDRONIC ACID; DISODIUM DISTYRYLBIPHENYL DISULFONATE; LIMONENE, (+)-; LINALOOL, (+/-)-; .ALPHA.-HEXYLCINNAMALDEHYDE; BENZYL SALICYLATE; GERANIOL; EUGENOL; ZINC OXIDE

Covex Antibacterial Bar Soap, Active Protection

Active ingredients

Benzalkonium Chloride 0.13%

Purpose

Antibacterial

Uses

- for handwashing to decrease bacteria on the skin

Warnings

For external use only

When using this product

- Do not use in the eyes.

Stop use and ask a doctor if

- irritation and redness develop. If condition persists for more than 72 hours consult a doctor.

Keep out of reach of children.

If swallowed, get medical help or contact a Poison Contrl Center right away.

Directions

- Wet hands and forearms. Apply to hands and foreams. Scrub thoroughly for 60 seconds. Rinse and repeat

Inactive ingredients:

Sodium Tallowate, Sodium palmate, Water, Sodium Palm Kernelate, Fragrance, Sodium Chloride, Glycerin, C 12-15 Alkyl Lactate, Titanium Dioxide, Tetrasodium EDTA, Etidronic Acid, Disodium Distrylbiphenyl Disulfonate, Limonene, Linalool, Hexyl Cinnamal, Benzyl Salicylate, geraniol, Eugenol.